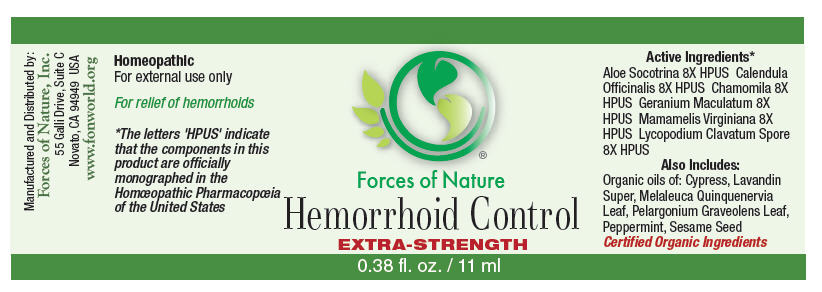 DRUG LABEL: Hemorrhoid Control 
NDC: 51393-6445 | Form: SOLUTION/ DROPS
Manufacturer: Forces of Nature
Category: homeopathic | Type: HUMAN OTC DRUG LABEL
Date: 20100824

ACTIVE INGREDIENTS: Aloe 8 [hp_X]/1000 mL; CALENDULA OFFICINALIS FLOWERING TOP 8 [hp_X]/1000 mL; Hamamelis virginiana Root Bark/Stem Bark 8 [hp_X]/1000 mL; Lycopodium clavatum Spore 8 [hp_X]/1000 mL; Chamomile 8 [hp_X]/1000 mL; Geranium Maculatum Root 8 [hp_X]/1000 mL

Hemorrhoid Control Extra Strength

Drug Facts

Indications

For relief for hemorrhoids

ACTIVE INGREDIENT

PURPOSE

Homeopathic Active Ingredients [The letters 'HPUS' indicate that the components in this product are officially monographed in the Homœopathic Pharmacopœia of the United States.]
Equal parts of: | Purpose
Aloe Socotrina 8X HPUS | Relief for hemorrhoids that are tender, sore, burning
Calendula Officinalis 8X HPUS | Promotes healthy skin and healing
Chamomilla 8X HPUS | Soothing for hemorrhoidal tissue
Geranium Maculatum 8X HPUS | Relief for skin ulcers
Mamamelis Virginiana 8X HPUS | Relief of hemorrhoids that are sore or burning
Lycopodium Clavatum Spore 8X HPUS | Relief for painful hemorrhoids

Also Contains Certified Organic Oils of

Cypress, Lavandin Super, Melaleuca Quinquenervia Leaf, Pelargonium Graveolens Leaf, Peppermint Oil, Sesame Seed

Directions

Moisten cotton ball with water, apply 2-3 drops of product. Dab onto treatment area 2-4 times per day until problem is gone.

Warnings

WHEN USING

Some individuals may be sensitive to essential oils. Begin with a small drop to determine if the product causes any increased redness or irritation and discontinue use if it irritates your skin.

PREGNANCY OR BREAST FEEDING

If you are pregnant or breast-feeding, ask a health professional before use.

DO NOT USE

For external use only. If accidental ingestion, get medical help or contact a Poison Control Center. Do not apply to the eyes; in the event of contact, flush with water and seek advice from medical personnel.

KEEP OUT OF REACH OF CHILDREN

Not to be used with children under 2 years of age. Keep all medicines out of the reach of children.

Stop use and ask a doctor if condition worsens, symptoms last more than 7 days, or clear up and occur again within a few days.

Manufactured by:
Forces of Nature, Inc.
55 Galli Drive, Suite C
Novato, CA 94949 USA
www.fonworld.org

Product questions?

877-975-3797

NDC#: 51393-6445-1 (11ml) // 51393-6445-2 (33ml)

PRINCIPAL DISPLAY PANEL - 11 ml Bottle Label

Forces of Nature

Hemorrhoid Control
EXTRA-STRENGTH

0.38 fl. oz. / 11 ml